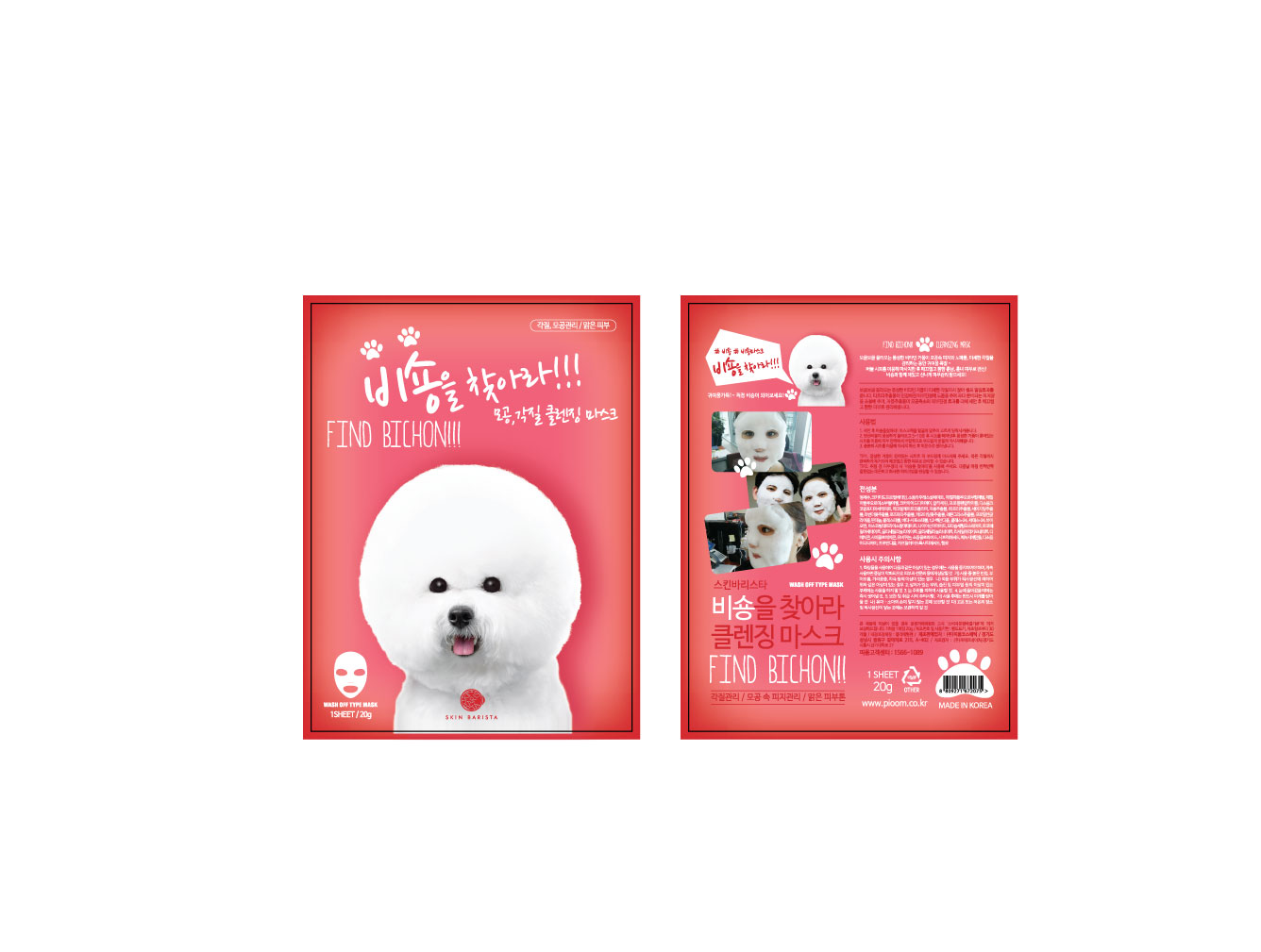 DRUG LABEL: FIND BICHON CLEANSING MASK
NDC: 70441-0005 | Form: LIQUID
Manufacturer: Pioom Cosmetic Co.,ltd
Category: otc | Type: HUMAN OTC DRUG LABEL
Date: 20170530

ACTIVE INGREDIENTS: GLYCERIN 1 g/100 g
INACTIVE INGREDIENTS: WATER

Drug Facts

ACTIVE INGREDIENT

GLYCERIN

INACTIVE INGREDIENT

Water
Cocamidopropyl Betaine
Sodium Lauryl Sulfate
Methyl Perfluorobutyl Ether
Methyl Perfluoroisobutyl Ether
Cocamide DEA
Propylene glycol
Disodium Cocoamphodiacetate
Acrylates Copolymer
Colloidal Gold
Citrus Paradisi (Grapefruit) Fruit Extract
Melaleuca Alternifolia (Tea Tree) Extract
Salvia Officinalis (Sage) Leaf Extract
Lavandula Angustifolia (Lavender) Flower Extract
Rosmarinus Officinalis (Rosemary) Extract
Chamomilla Recutita (Matricaria) Flower Extract
Cymbopogon Schoenanthus Extract
Panthenol
Cholesterol
Beta-Sitosterol
1,2-Hexanediol
Choleth-24
Ceteth-24
Biotin
Ascorbyl Tetraisopalmitate
Niacinamide
Potassium Cetyl Phosphate
Tocopheryl Acetate
Glyceryl Linoleate
Glyceryl Linolenate
Glyceryl Arachidonate
Dimethicone
Cyclomethicone
Ubiquinone
Sodium Chloride
Citric Acid
Phenoxyethanol
Disodium EDTA
Propanediol
Caprylhydroxamic Acid
Fragrance

PURPOSE

Dead skin cell, pore control

keep out of reach of the children

INDICATIONS AND USAGE

Clean the skin thoroughly before using this product.

Apply the mask over cleansed face and leave on for 5 to 10 minutes, allowing the sparkling bubbles to fully rise.

Peel off the mask, and gently massage the skin using the residual bubbles.

Finish by rinsing with warm water. For best results, repeat twice a week.

WARNINGS

1. If the following symptoms occur after product use, stop using the product immediately and consult a dermatologist (continuous use can exacerbate the symptoms).
1) Occurrence of red spots, swelling, itchiness, and other skin irritation
2) If the symptoms above occur after the application area is exposed to direct sunlight
2. Do not use on open wounds, eczema, and other skin irritations
3. Precaution for Storage and Handling
1) Close the lid after use
2) Keep out of reach of infants and children
3) Do not to store in a place with high/low temperature and exposed to direct sunlight

4. Use as avoiding eye areas.

DOSAGE AND ADMINISTRATION

for external use only